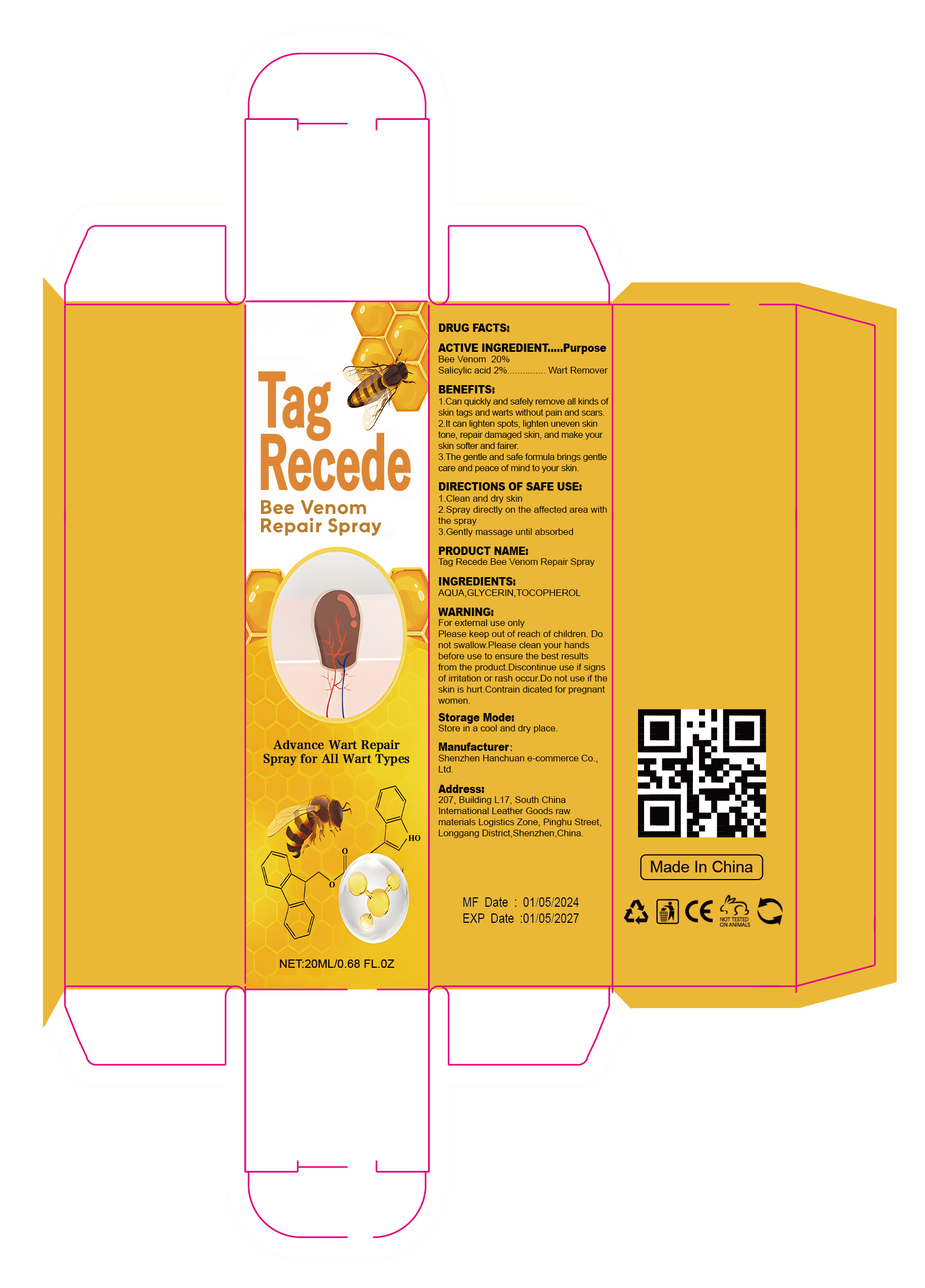 DRUG LABEL: Tag Recede Bee Venom RepairSpray
NDC: 84302-004 | Form: LIQUID
Manufacturer: Shenzhen Hanchuan e-commerce Co., Ltd
Category: otc | Type: HUMAN OTC DRUG LABEL
Date: 20240515

ACTIVE INGREDIENTS: SALICYLIC ACID 2 g/100 mL; APIS MELLIFERA VENOM 20 g/100 mL
INACTIVE INGREDIENTS: TOCOPHEROL; WATER; GLYCERIN

Tag Recede Bee Venom Repair Spray

ACTIVE INGREDIENT

BEE VENOM 20%

Salicylic acid 2%

PURPOSE

Wart Remover

Please keep out of reach of children

INDICATIONS AND USAGE

1.Can quickly and safely remove all kinds ofskin tags and warts without pain and scars.
2.lt can lighten spots, lighten uneven skintone, repair damaged skin, and make yourskin softer and fairer
3.The gentle and safe formula brings gentlecare and peace of mind to your skin

WARNINGS

For external use only
Please keep out of reach of children.
Donot swallow.Please clean your handsbefore use to ensure the best resultsfrom the product.
Discontinue use if signsof irritation or rash occur.
Do not use if theskin is hurt.
Contrain dicated for pregnantwomen

DOSAGE AND ADMINISTRATION

1.Clean and dry skin
2.Spray directly on the affected area withthe spray
3.Gently massage until absorbed

STORAGE AND HANDLING

Store in a cool and dry place.

INACTIVE INGREDIENT

AQUA
GLYCERIN
TOCOPHEROL